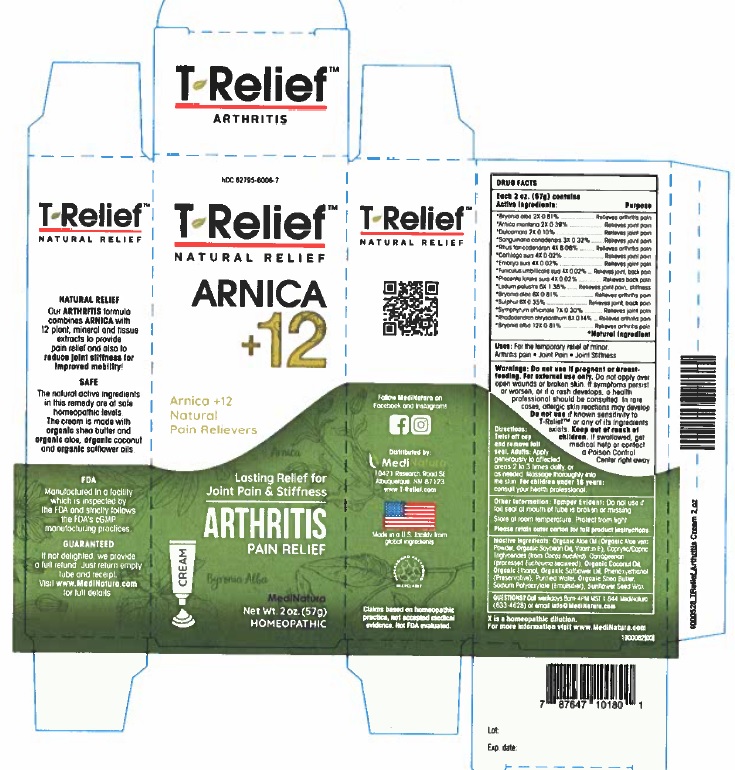 DRUG LABEL: T-Relief Arthritis
NDC: 62795-6006 | Form: CREAM
Manufacturer: MediNatura Inc
Category: homeopathic | Type: HUMAN OTC DRUG LABEL
Date: 20230928

ACTIVE INGREDIENTS: ARNICA MONTANA ROOT 2 [hp_X]/1 g; BRYONIA ALBA WHOLE 2 [hp_X]/1 g; SUS SCROFA UMBILICAL CORD 4 [hp_X]/1 g; SOLANUM DULCAMARA TOP 2 [hp_X]/1 g; SUS SCROFA EMBRYO 4 [hp_X]/1 g; SUS SCROFA CARTILAGE 4 [hp_X]/1 g; LEDUM PALUSTRE TWIG 6 [hp_X]/1 g; SUS SCROFA PLACENTA 4 [hp_X]/1 g; RHODODENDRON AUREUM LEAF 8 [hp_X]/1 g; TOXICODENDRON PUBESCENS LEAF 4 [hp_X]/1 g; SANGUINARIA CANADENSIS ROOT 3 [hp_X]/1 g; SULFUR 6 [hp_X]/1 g; COMFREY ROOT 7 [hp_X]/1 g
INACTIVE INGREDIENTS: ALOE; SOYBEAN OIL; CAPRYLIC/CAPRIC/LAURIC TRIGLYCERIDE; CARRAGEENAN; COCONUT OIL; SAFFLOWER OIL; ISOHEXADECANE; PEG-8 DIMETHICONE ; PHENOXYETHANOL; POTASSIUM SORBATE; WATER; ALCOHOL; SHEA BUTTER; SODIUM POLYACRYLATE (8000 MW)

T-Relief Arthritis Cream

Active Ingredients

Each 50g contains

Active ingredients Purpose

*Arnica montana 2X 0.39%...............Relieves joint pain

*Bryonia alba 2X 0.81%.............................Relieves arthritis pain

*Bryonia alba 6X 0.81%.............................Relieves arthritis pain

*Bryonia alba 12X 0.81%...........................Relieves arthritis pain

*Cartilago suis 4X 0.02%............................Relieves joint pain

*Dulcamara 2X 0.10%................................Relieves joint pain

*Embryo suis 4X 0.02%.............................Relieves joint pain

*Funiculus umbilicalis suis 4X 0.02%............Relieves joint, back pain

*Ledum palustre 6X 1.38%.........................Relieves joint pain, stiffness

*Placenta totalis suis 4X 0.02%...................Relieves back pain

*Rhododendron chrysanthum 8X 0.14%......Relieves arthritis pain

*Rhus toxicodendron 4X 8.08%...................Relieves arthritis pain

*Sanguinaria canadensis 3X 0.32%...............Relieves joint pain

*Sulphur 6X 0.35%. ....................................Relieves joint back, pain

*Symphytum officinale 7X 0.30%.................Relieves joint pain

*Natural Ingredients

Uses

For the temporary relief of minor: Arthritis Pain • Joint Pain • Joint Stiffness.

WARNINGS

Do not use if pregnant or breast-feeding. For external use only.Do not apply over open wounds or broken skin. If symptoms persist or worsen, or if a rash develops, a health professional should be consulted. In rare cases, allergic skin reactions may develop. Do not use if known sensitivity to T-ReliefTM Arthritis or any of its ingredients exists. Keep out of reach of children. If swallowed, get medical help or contact a Poison Control Center right away.

DIRECTIONS

Twist off cap and remove the foil seal. Adults: Apply generously to affected areas 2-3 times daily or, as needed. Massage thoroughly into the skin. For children under 18 years, consult your health professional.

INACTIVE INGREDIENTS

Organic Aloe Oil (Organic Aloe vera Powder, Organic Soybean Oil, Vitamin E), Caprylic/Capric Triglycerides (from Cocos nucifera), Carrageenan (processed Eucheuma seaweed), Organic Coconut Oil, Ethanol (from Organic Cane), Organic Safflower Oil, Phenoxyethanol (Preservative), Purified Water, Organic Shea Butter, Sodium Polyacrylate (Emulsifier), Natural Sunflower Seed Wax

KEEP OUT OF REACH OF CHILDREN

PURPOSE

Relieves

• Arthritis Pain

• Joint Pain

• Joint Stiffness